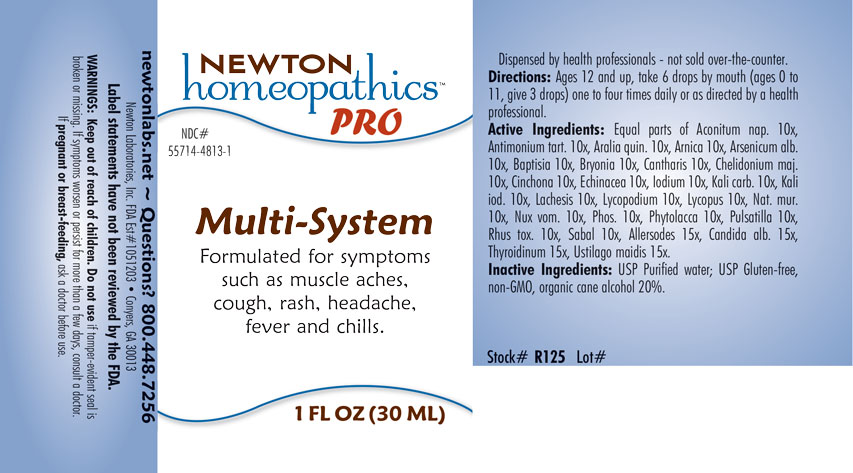 DRUG LABEL: Multi-System
NDC: 55714-4813 | Form: LIQUID
Manufacturer: Newton Laboratories, Inc.
Category: homeopathic | Type: HUMAN OTC DRUG LABEL
Date: 20201204

ACTIVE INGREDIENTS: ACONITUM NAPELLUS 10 [hp_X]/1 mL; PHOSPHORUS 10 [hp_X]/1 mL; AMERICAN GINSENG 10 [hp_X]/1 mL; ARNICA MONTANA 10 [hp_X]/1 mL; ARSENIC TRIOXIDE 10 [hp_X]/1 mL; BAPTISIA TINCTORIA ROOT 10 [hp_X]/1 mL; BRYONIA ALBA ROOT 10 [hp_X]/1 mL; LYTTA VESICATORIA 10 [hp_X]/1 mL; CHELIDONIUM MAJUS 10 [hp_X]/1 mL; CINCHONA OFFICINALIS BARK 10 [hp_X]/1 mL; ECHINACEA, UNSPECIFIED 10 [hp_X]/1 mL; IODINE 10 [hp_X]/1 mL; POTASSIUM CARBONATE 10 [hp_X]/1 mL; POTASSIUM IODIDE 10 [hp_X]/1 mL; LACHESIS MUTA VENOM 10 [hp_X]/1 mL; LYCOPODIUM CLAVATUM SPORE 10 [hp_X]/1 mL; LYCOPUS VIRGINICUS 10 [hp_X]/1 mL; SODIUM CHLORIDE 10 [hp_X]/1 mL; STRYCHNOS NUX-VOMICA SEED 10 [hp_X]/1 mL; SAW PALMETTO 10 [hp_X]/1 mL; ANTIMONY POTASSIUM TARTRATE 10 [hp_X]/1 mL; USTILAGO MAYDIS 15 [hp_X]/1 mL; CLADOSPORIUM HERBARUM 15 [hp_X]/1 mL; ANEMONE PULSATILLA 10 [hp_X]/1 mL; ASPERGILLUS NIGER VAR. NIGER 15 [hp_X]/1 mL; CANDIDA ALBICANS 15 [hp_X]/1 mL; THYROID, UNSPECIFIED 15 [hp_X]/1 mL; PHYTOLACCA AMERICANA ROOT 10 [hp_X]/1 mL; TOXICODENDRON PUBESCENS LEAF 10 [hp_X]/1 mL
INACTIVE INGREDIENTS: WATER; ALCOHOL

Multi 4813L

INDICATIONS & USAGE SECTION

Formulated for symptoms such as muscle aches, cough, rash, headache, fever and chills.

DOSAGE & ADMINISTRATION SECTION

Directions: Ages 12 and up, take 6 drops by mouth (ages 0 to 11, give 3 drops) one to four times daily or as directed by a health professional.

OTC - ACTIVE INGREDIENT SECTION

Equl parts of Aconitum napellus 10x, Antimonium tartaricum 10x, Aralia quinquefolia 10x, Arnica montana 10x, Arsenicum album 10x, Baptisia tinctoria 10x, Bryonia 10x, Cantharis 10x, Chelidonium majus 10x, Cinchona officinalis 10x, Echinacea 10x, Iodium 10x, Kali carbonicum 10x, Kali iodatum 10x, Lachesis mutus 10x, Lycopodium clavatum 10x, Lycopus virginicus 10x, Natrum muriaticum 10x, Nux vomica 10x, Phosphorus 10x, Phytolacca decandra 10x, Pulsatilla 10x, Rhus toxicodendron 10x, Sabal serrulata 10x, Allersodes 15x, Candida albicans 15x, Thyroidinum 15x, Ustilago maidis 15x.

OTC - PURPOSE SECTION

Formulated for symptoms such as muscle aches, cough, rash, headache, fever and chills

INACTIVE INGREDIENT SECTION

Inactive Ingredients: USP Purified Water; USP Gluten-free, non-GMO, organic cane alcohol 20%.

QUESTIONS SECTION

newtonlabs.net - Questions? 800.448.7256

Newton Laboratories, Inc. FDA Est # 1051203 Conyers, GA 30013

WARNINGS SECTION

WARNINGS: Keep out of reach of children. Do not use if tamper-evident seal is broken or missing. If symptoms worsen or persist for more than a few days, consult a doctor. If pregnant or breast-feeding, ask a doctor before use.

OTC - PREGNANCY OR BREAST FEEDING SECTION

If pregnant or breast-feeding, ask a doctor before use.

OTC - KEEP OUT OF REACH OF CHILDREN SECTION

Keep out of reach of children.